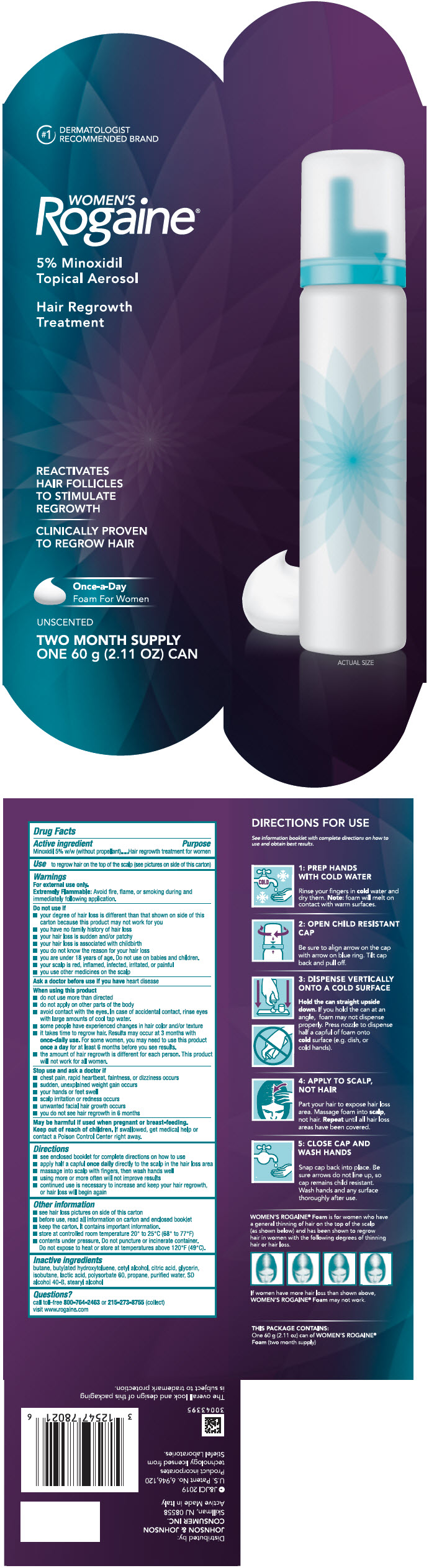 DRUG LABEL: Womens Rogaine Unscented
NDC: 69968-0030 | Form: AEROSOL, FOAM
Manufacturer: Kenvue Brands LLC
Category: otc | Type: HUMAN OTC DRUG LABEL
Date: 20241113

ACTIVE INGREDIENTS: MINOXIDIL 50 mg/1 g
INACTIVE INGREDIENTS: BUTANE; BUTYLATED HYDROXYTOLUENE; CETYL ALCOHOL; CITRIC ACID MONOHYDRATE; GLYCERIN; ISOBUTANE; LACTIC ACID, UNSPECIFIED FORM; POLYSORBATE 60; PROPANE; WATER; ALCOHOL; STEARYL ALCOHOL

WOMEN's Rogaine® UNSCENTED

Drug Facts

Active ingredient

Minoxidil 5% w/w (without propellant)

Purpose

Hair regrowth treatment for women

Use

to regrow hair on the top of the scalp (see pictures on side of this carton)

Warnings

For external use only.

Extremely Flammable

Avoid fire, flame, or smoking during and immediately following application.

Do not use if

- your degree of hair loss is different than that shown on side of this carton because this product may not work for you
- you have no family history of hair loss
- your hair loss is sudden and/or patchy
- your hair loss is associated with childbirth
- you do not know the reason for your hair loss
- you are under 18 years of age. Do not use on babies and children.
- your scalp is red, inflamed, infected, irritated, or painful
- you use other medicines on the scalp

Ask a doctor before use if you have heart disease

When using this product

- do not use more than directed
- do not apply on other parts of the body
- avoid contact with the eyes. In case of accidental contact, rinse eyes with large amounts of cool tap water.
- some people have experienced changes in hair color and/or texture
- it takes time to regrow hair. Results may occur at 3 months with once daily use. For some women, you may need to use this product once a day for at least 6 months before you see results.
- the amount of hair regrowth is different for each person. This product will not work for all women.

Stop use and ask a doctor if

- chest pain, rapid heartbeat, faintness, or dizziness occurs
- sudden, unexplained weight gain occurs
- your hands or feet swell
- scalp irritation or redness occurs
- unwanted facial hair growth occurs
- you do not see hair regrowth in 6 months

PREGNANCY OR BREAST FEEDING

May be harmful if used when pregnant or breast-feeding.

Keep out of reach of children. If swallowed, get medical help or contact a Poison Control Center right away.

Directions

- see enclosed booklet for complete directions on how to use
- apply half a capful once daily directly to the scalp in the hair loss area
- massage into scalp with fingers, then wash hands well
- using more or more often will not improve results
- continued use is necessary to increase and keep your hair regrowth, or hair loss will begin again

Other information

- see hair loss pictures on side of this carton
- before use, read all information on carton and enclosed booklet
- keep the carton. It contains important information.
- store at controlled room temperature 20º to 25º C (68º to 77º F)
- contents under pressure. Do not puncture or incinerate container. Do not expose to heat or store at temperatures above 120°F (49°C).

Inactive ingredients

butane, butylated hydroxytoluene, cetyl alcohol, citric acid, glycerin, isobutane, lactic acid, polysorbate 60, propane, purified water, SD alcohol 40-B, stearyl alcohol

Questions?

call toll-free 800-764-2463 or 215-273-8755 (collect)
visit www.rogaine.com

Distributed by:
JOHNSON & JOHNSON
CONSUMER INC.
Skillman, NJ 08558

PRINCIPAL DISPLAY PANEL - 60 g Can Carton

#1 DERMATOLOGIST
RECOMMENDED BRAND

WOMEN'S
Rogaine®

5% Minoxidil
Topical Aerosol

Hair Regrowth
Treatment

REACTIVATES
HAIR FOLLICLES
TO STIMULATE
REGROWTH

CLINICALLY PROVEN
TO REGROW HAIR

Once-a-Day
Foam For Women

UNSCENTED

TWO MONTH SUPPLY
ONE 60 g (2.11 OZ) CAN